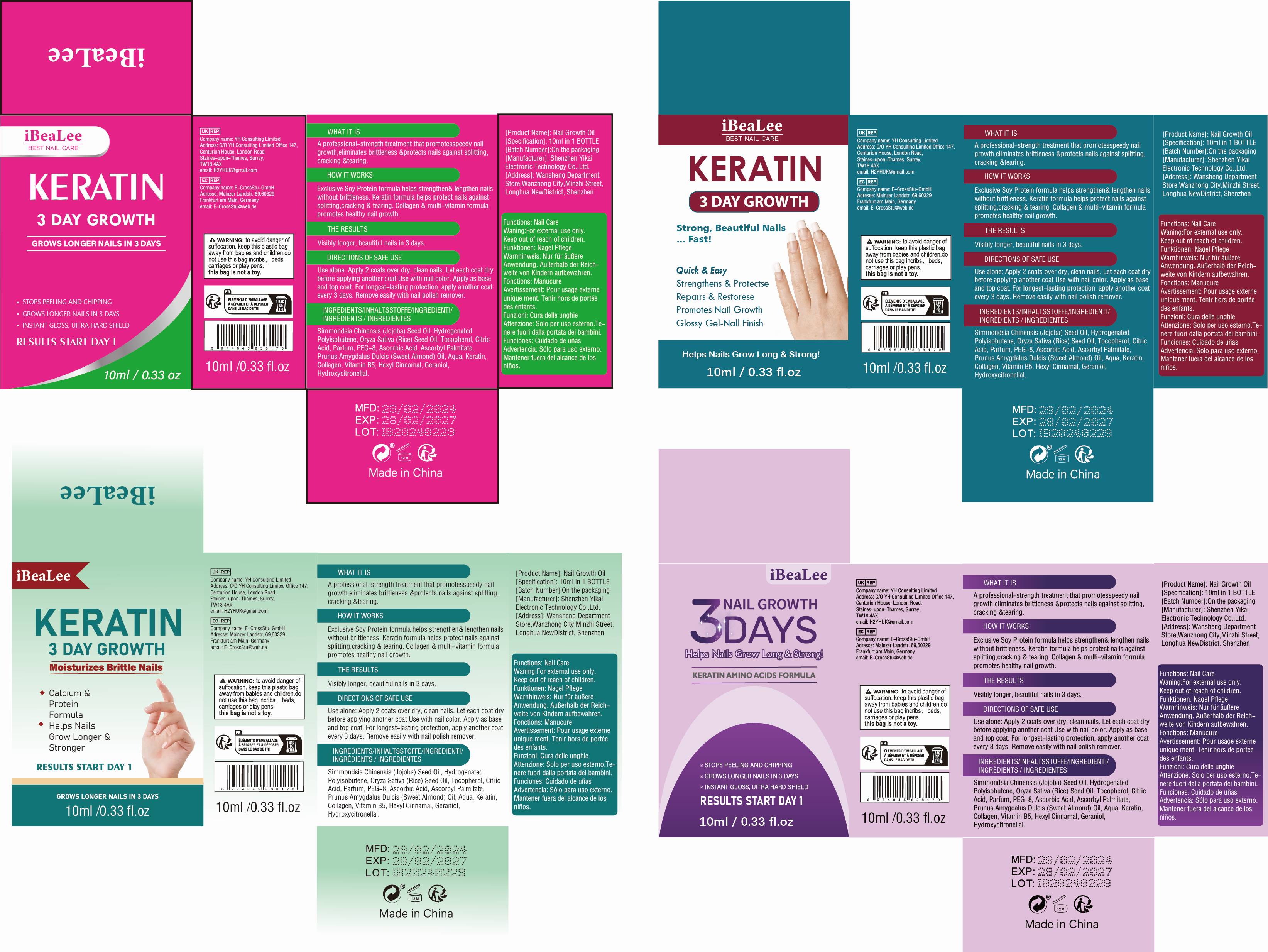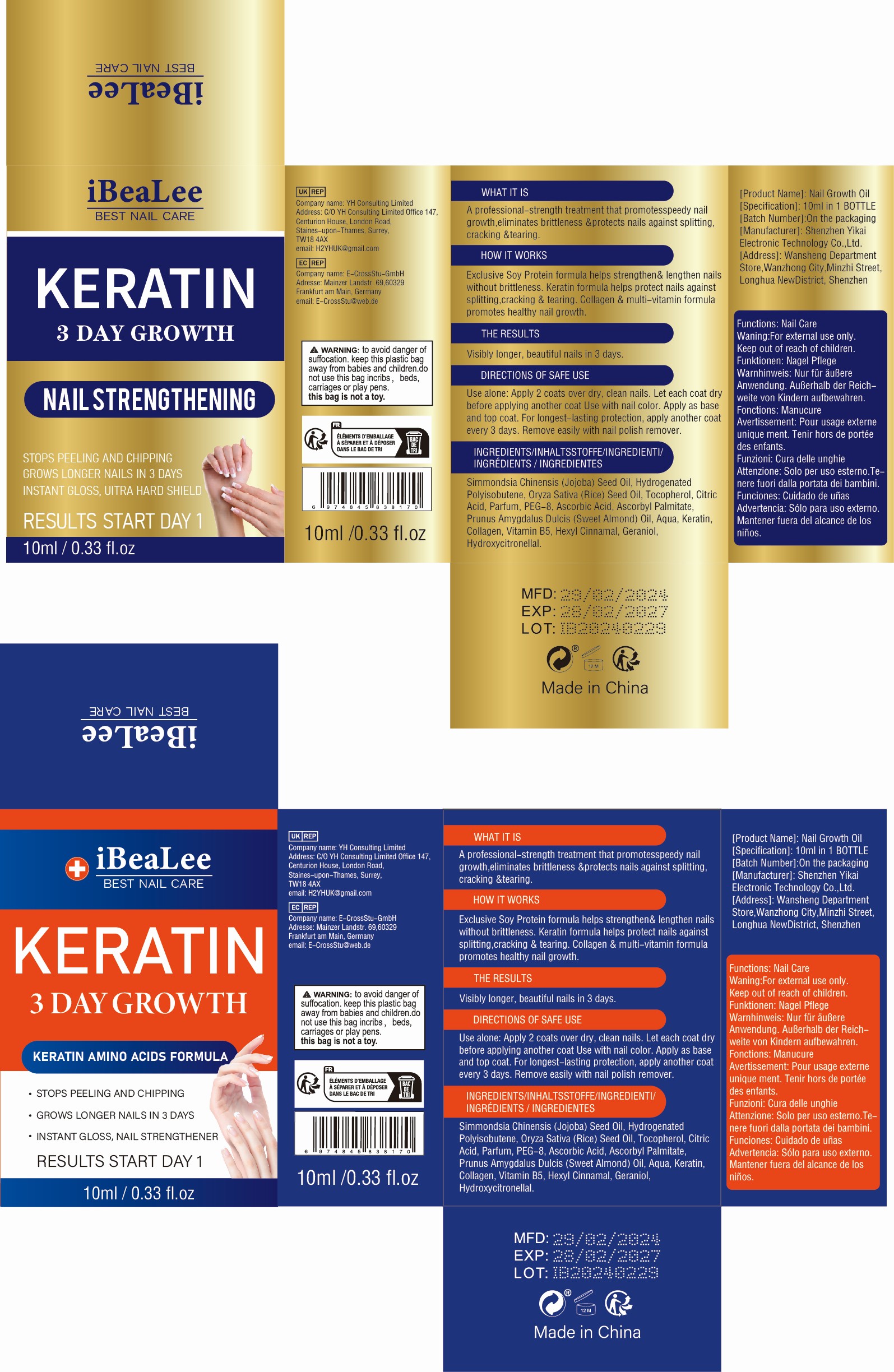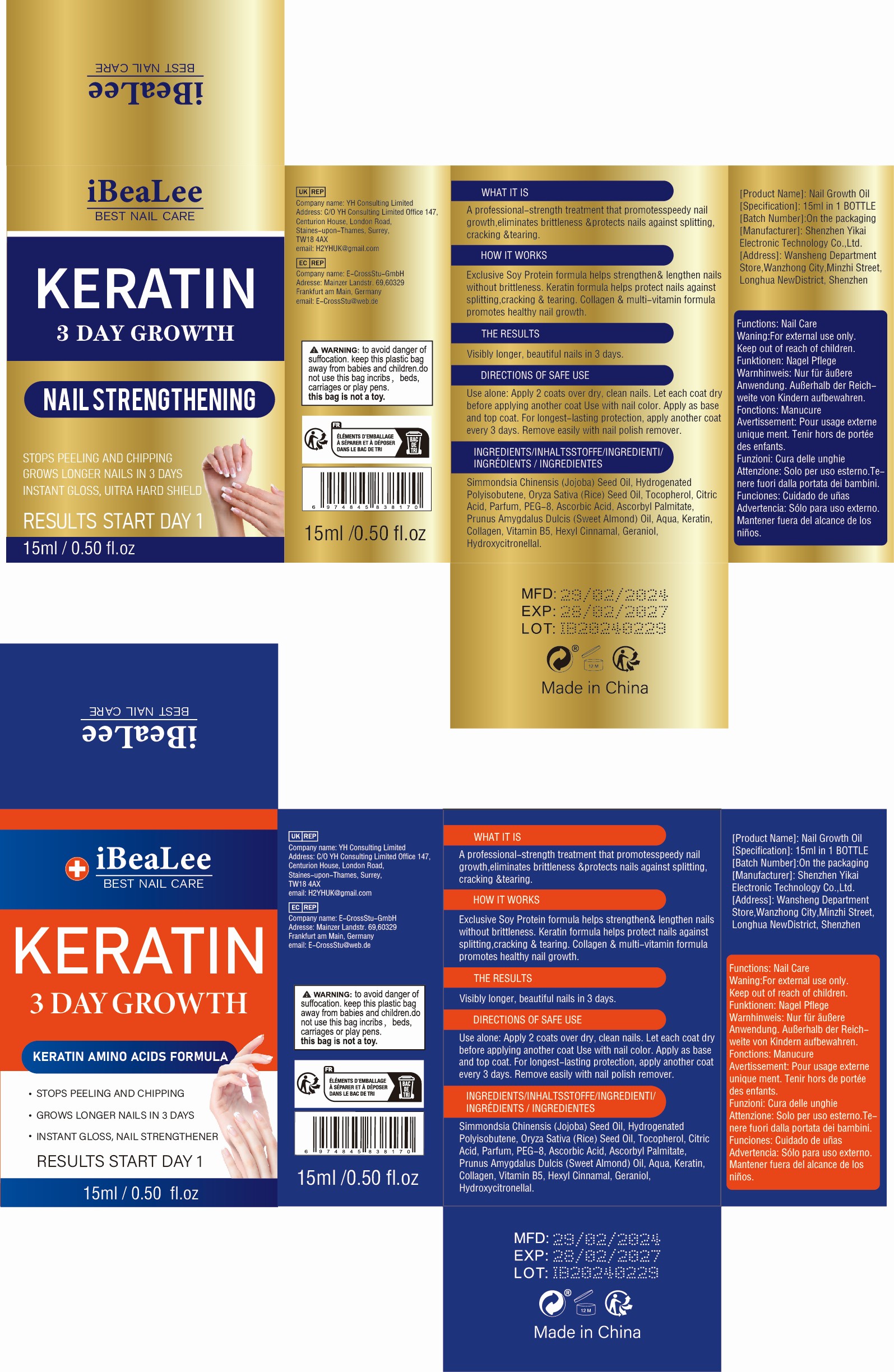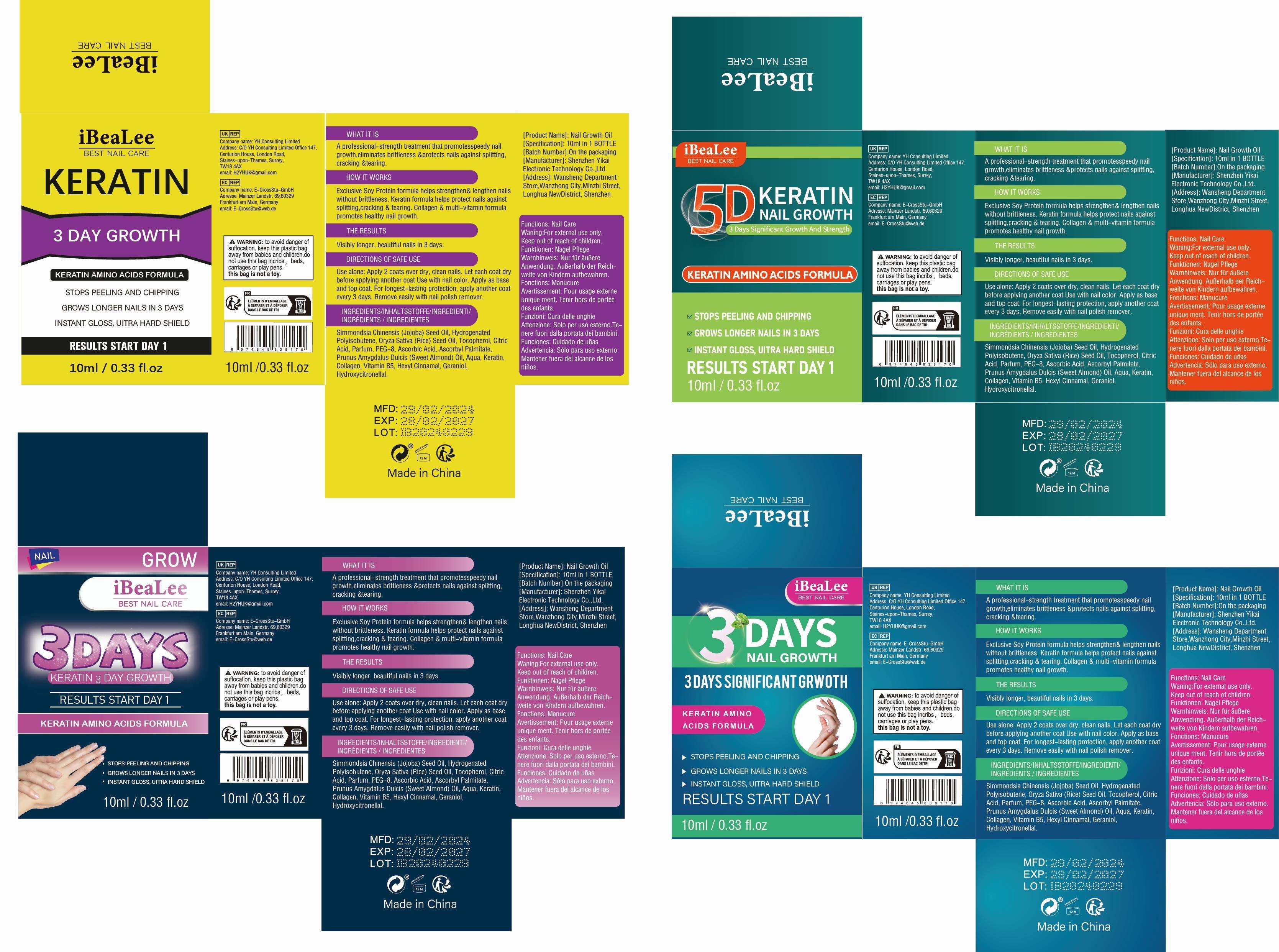 DRUG LABEL: Nail Growth Oil
NDC: 84117-005 | Form: OIL
Manufacturer: Shenzhen Hengkaifeng Commerce and Trade Co., Ltd
Category: otc | Type: HUMAN OTC DRUG LABEL
Date: 20240410

ACTIVE INGREDIENTS: HAIR KERATIN AMINO ACIDS 5 g/100 mL
INACTIVE INGREDIENTS: CITRIC ACID MONOHYDRATE; HYDROGENATED POLYISOBUTENE (450 MW); RICE OIL; TOCOPHEROL; JOJOBA OIL; COLLAGEN ALPHA-1(XIV) CHAIN

ACTIVE INGREDIENT

Keratin 5%

Purpose

nail growth

Use

A professional-strength treatment that promotesspeedy nail
growth,eliminates brittleness &protects nails against splitting,
cracking &tearing.

WarningS

For external use only.

For external use only.

Stop use and ask a doctor

if rash or irritation develops and lasts.

Keep out of reach of children

If product is swallowed, get medical help or contact a Poison Control
Center right away.

Directions Of Safe Use

Use alone: Apply 2 coats over dry, clean nails. Let each coat dry
before applying another coat Use with nail color. Apply as base
and top coat. For longest-lasting protection, apply another coat
every 3 days. Remove easily with nail polish remover.

Inactive ingredients

Simmondsia Chinensis (Jojoba) Seed Oil, Hydrogenated
Polyisobutene, Oryza Sativa (Rice) Seed Oil, Tocopherol, Citric
Acid, Parfum, PEG-8, Ascorbic Acid, Ascorbyl Palmitate,
Prunus Amygdalus Dulcis (Sweet Almond) Oil, Aqua,
Collagen, Vitamin B5, Hexyl Cinnamal, Geraniol,
Hydroxycitronellal.